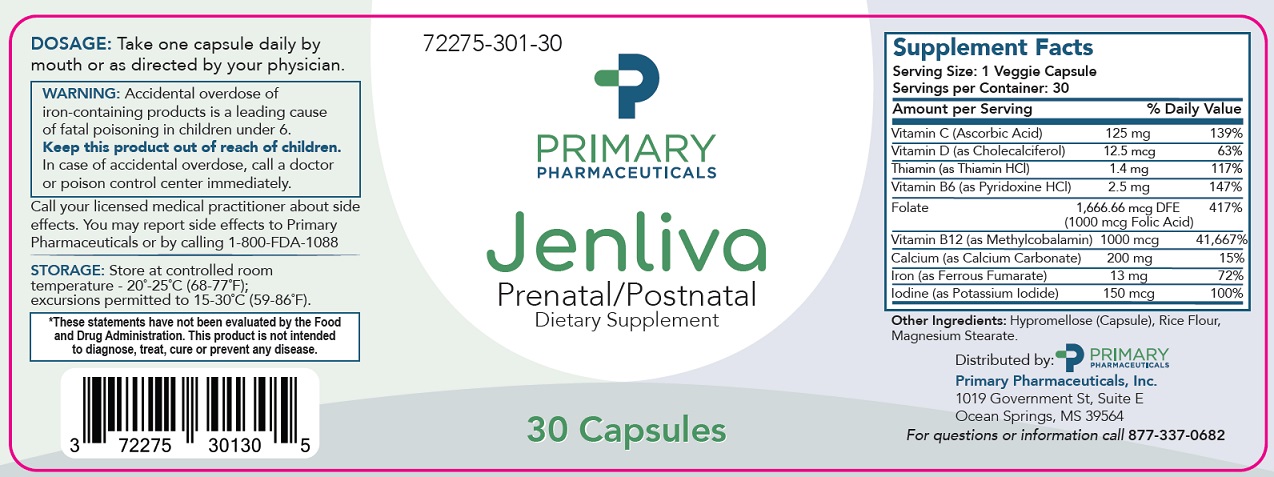 DRUG LABEL: Jenliva
NDC: 72275-301 | Form: CAPSULE
Manufacturer: Primary Pharmaceuticals, Inc.
Category: other | Type: Dietary Supplement
Date: 20210703

ACTIVE INGREDIENTS: ASCORBIC ACID 125 mg/1 1; CHOLECALCIFEROL 0.0125 mg/1 1; THIAMINE HYDROCHLORIDE 1.4 mg/1 1; PYRIDOXINE HYDROCHLORIDE 2.5 mg/1 1; FOLIC ACID 1 mg/1 1; METHYLCOBALAMIN 1 mg/1 1; CALCIUM CARBONATE 200 mg/1 1; FERROUS FUMARATE 13 mg/1 1; POTASSIUM IODIDE 0.15 mg/1 1
INACTIVE INGREDIENTS: HYPROMELLOSE, UNSPECIFIED; BROWN RICE; MAGNESIUM STEARATE

Jenliva

HEALTH CLAIM:

Jenliva Capsules - Prenatal/Postnatal Dietary Supplement

Dispensed by Prescription

Supplement Facts
Serving Size: 1 Capsule Serving per Bottle: 30
Amount Per Serving: |  | % Daily Value
Vitamin C (Ascorbic Acid) | 125 mg | 139%
Vitamin D (as Cholecalciferol) | 12.5 mcg | 63%
Thiamin (as Thiamin HCl) | 1.4 mg | 117%
Vitamin B6 (as Pyridoxine HCl) | 2.5 mg | 147%
Folate | 1,666 mcg DFE (1000 mcg Folic Acid) | 417%
Vitamin B12 (as Methylcobalamin) | 1,000 mcg | 41,667%
Calcium (from Calcium Carbonate) | 200 mg | 15%
Iron (as Ferrous Fumarate) | 13 mg | 72%
Iodine (as Potassium Iodide) | 150 mcg | 100%

OTHER INGREDIENTS: Hypromellose (Capsule), Rice Flour, and Magnesium Stearate.

DESCRIPTION:

Jenliva capsules are a prescription dietary supplement for use throughout pregnancy, during the postnatal period for both lactating and non-lactating mothers, and throughout the childbearing years. Jenliva capules may be useful in improving the nutritional status of women prior to conception.

WARNING AND PRECAUTIONS

WARNING: Accidental overdose of iron-containing products is a leading cause of fatal poisoning in children under 6. KEEP THIS AND ALL DRUGS OUT OF THE REACH OF CHILDREN. In case of accidental overdose, call a doctor or poison control center immediately.

CONTRAINDICATIONS:

Jenliva capsules are contraindicated in patients with a known hypersensitivity to any of the ingredients. Do not take this product if you are presently taking mineral oil, unless directed by a doctor.

PRECAUTIONS

PRECAUTION:

Folic acid alone is improper therapy in the treatment of pernicious anemia and other megaloblastic anemias where vitamin B is deficient. Folic acid in doses above 1 mg daily may obscure pernicious anemia in that hematologic remission can occur while neurological manifestations progress. Jenliva capsules should only be used under the direction and supervision of a licensed medical practitioner.

ADVERSE REACTIONS:

Allergic sensitization has been reported following both oral and parenteral administration of folic acid. You may report side effects by calling the FDA at 1-800-FDA-1088.

DOSAGE & ADMINISTRATION:

Usual adult dose is 1 capsule taken orally once or twice daily or as prescribed by a licensed medical practitioner.

HOW SUPPLIED HEALTH CLAIM:

Jenliva capsules are available as clear, standard-sized capsules and are available in 30-count bottles (72275-0301-30*). This product is not an Orange Book product.

Dispensed by Prescription†

Manufactured for: Primary Pharmaceuticals, Inc Ocean Springs, MS 39564

Rev. 10/20

*Primary Pharmaceuticals, Inc does not represent these product codes to be National Drug Codes (NDC). Product codes are formatted according to standard industry practice, to meet the formatting requirement by pedigree reporting and supply-chain control including pharmacies. †This product is a prescription-folate with or without other dietary ingredients that – due to increased folate levels increased risk associated with masking of B12 deficiency (pernicious anemia) requires administration under the care of a licensed medical practitioner (61 FR 8760). 1-3 The most appropriate way to ensure pedigree reporting consistent with these regulatory guidelines and safety monitoring is to dispense this product only by prescription. This is not an Orange Book product. This product may be administered only under a physician’s supervision and all prescriptions using this product shall be pursuant to state statutes as applicable. The ingredients, indication
or claims of this product are not to be construed to be drug claims. 1. Federal Register Notice of August 2, 1973 (38 FR 20750) 2. Federal Register Notice of October 17, 1980 (45 FR 69043, 69044) 3. Federal Register Notice of March 5, 1996 (61 FR 8760)

STORAGE AND HANDLING:

Store at 20°-25°C (68°-77°F); excursions permitted to 15°-30°C (59°-86°F) [See USP Controlled Room Temperature.] Protect from heat, light and moisture. Tamper Evident: Do not use if seal is broken or missing.

Distributed by: Primary Pharmaceuticals, Inc , Ocean Springs, MS 39564.

PRINCIPAL DISPLAY PANEL

Jenliva

Prenatal/Postnatal

Dietary Supplement